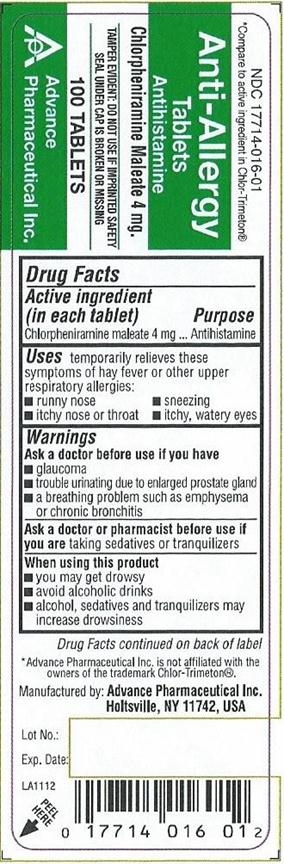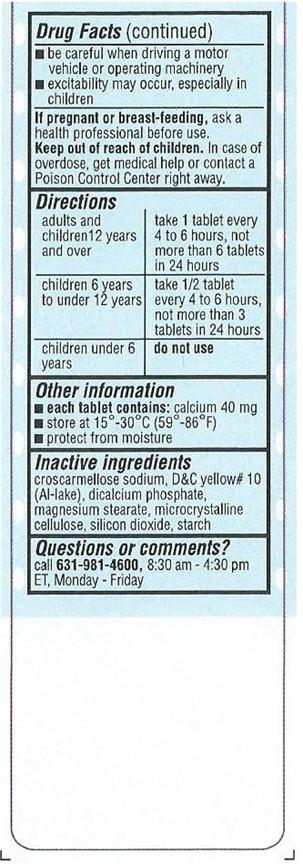 DRUG LABEL: Anti Allergy
NDC: 17714-016 | Form: TABLET
Manufacturer: Advance Pharmaceutical Inc.
Category: otc | Type: HUMAN OTC DRUG LABEL
Date: 20171030

ACTIVE INGREDIENTS: CHLORPHENIRAMINE MALEATE 4 mg/1 1
INACTIVE INGREDIENTS: CROSCARMELLOSE SODIUM; D&C YELLOW NO. 10; ANHYDROUS DIBASIC CALCIUM PHOSPHATE; MAGNESIUM STEARATE; CELLULOSE, MICROCRYSTALLINE; STARCH, CORN; SILICON DIOXIDE

Anti-Allergy Tablets Antihistamine

Active Ingredient

(in each tablet)

Chlorpheniramine Maleate 4 mg

Purpose

Antihistamine

Uses

temporarily relieves these symptoms of hay fever or other upper respiratory allergies :

- runny nose
- itchy nose or throat
- sneezing
- itchy, watery eyes

Warnings

Ask a doctor before use if you have

- glaucoma
- trouble urinating due to an enlarged prostate gland
- a breathing problem such as emphysema or chronic bronchitis

Ask a doctor or pharmacist before use if you are taking sedatives or tranquilizers

When using this product

- you may get drowsy
- avoid alcoholic drinks
- alcohol, sedatives & tranquilizers may increase drowsiness
- be careful when driving a motor vehicle or operating a machine
- excitability may occur, especially in children
  If pregnant or breast-feeding, ask a health professional before use.

Keep Out of Reach of Children

In case of overdose, get medical help or contact a Poison Control Center right away.

Directions[/S]

Adults & children 12 years and over | take 1 tablet every 4 to 6 hours, not more than 6 tablets in 24 hours
children 6 years to under 12 years | take ½ tablet every 4 to 6 hours not more than 3 tablets in 24 hours
children under 6 years | do not use

Other Information

- each tablet contains: calcium 40 mg
- store between 15°-30°C (59°-86°F)
- protect from moisture

Inactive Ingredients

croscarmellose sodium, D&C yellow #10 (al-lake), dicalcium phosphate, magnesium stearate, microcrystalline cellulose, silicon dioxide, starch

Questions or Comments

Call 1-800-645-2158, 8.30 am – 4.30 pm ET, Monday - Friday

TAMPER EVIDENT: DO NOT USE IF CARTON IS OPENED OR BLISTER UNIT IS BROKEN OR DAMAGED

PACKAGE LABEL.PRINCIPAL DISPLAY PANEL

Chlorpheniramine Maleate 4 mg
Antihistamine

17714-016-01 100 Tablets